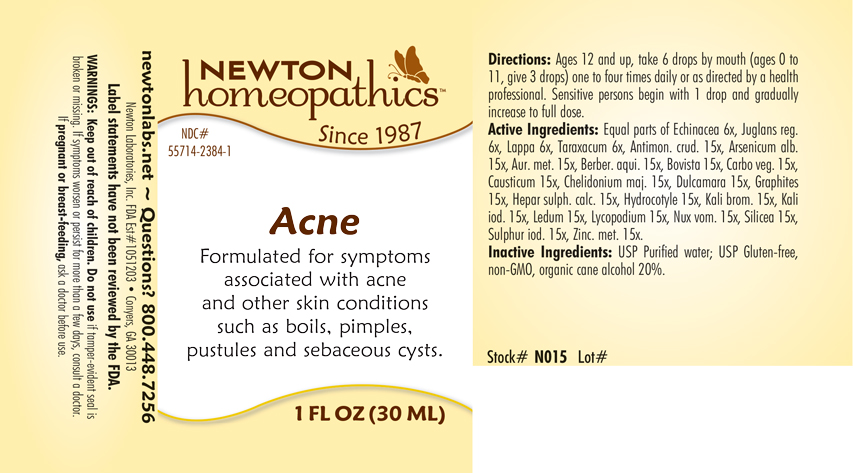 DRUG LABEL: Acne
NDC: 55714-2384 | Form: LIQUID
Manufacturer: Newton Laboratories, Inc.
Category: homeopathic | Type: HUMAN OTC DRUG LABEL
Date: 20201124

ACTIVE INGREDIENTS: ANTIMONY TRISULFIDE 15 [hp_X]/1 mL; ARSENIC CATION (3+) 15 [hp_X]/1 mL; GOLD 15 [hp_X]/1 mL; MAHONIA AQUIFOLIUM ROOT BARK 15 [hp_X]/1 mL; GIANT PUFFBALL 15 [hp_X]/1 mL; ACTIVATED CHARCOAL 15 [hp_X]/1 mL; CAUSTICUM 15 [hp_X]/1 mL; CHELIDONIUM MAJUS 15 [hp_X]/1 mL; SOLANUM DULCAMARA TOP 15 [hp_X]/1 mL; GRAPHITE 15 [hp_X]/1 mL; CALCIUM SULFIDE 15 [hp_X]/1 mL; CENTELLA ASIATICA 15 [hp_X]/1 mL; POTASSIUM BROMIDE 15 [hp_X]/1 mL; POTASSIUM IODIDE 15 [hp_X]/1 mL; LEDUM PALUSTRE TWIG 15 [hp_X]/1 mL; LYCOPODIUM CLAVATUM SPORE 15 [hp_X]/1 mL; STRYCHNOS NUX-VOMICA SEED 15 [hp_X]/1 mL; SILICON DIOXIDE 15 [hp_X]/1 mL; SULFUR IODIDE 15 [hp_X]/1 mL; ZINC 15 [hp_X]/1 mL; ECHINACEA, UNSPECIFIED 6 [hp_X]/1 mL; ENGLISH WALNUT 6 [hp_X]/1 mL; ARCTIUM LAPPA ROOT 6 [hp_X]/1 mL; TARAXACUM OFFICINALE 6 [hp_X]/1 mL
INACTIVE INGREDIENTS: ALCOHOL; WATER

Acne 2384L

OTC - KEEP OUT OF REACH OF CHILDREN SECTION

Keep out of reach of children.

OTC - PREGNANCY OR BREAST FEEDING SECTION

If pregnant or breat-feeding, ask a doctor before use.

WARNINGS SECTION

WARNINGS: Keep out of reach of children. Do not use if tamper-evident seal is broken or missing. If symptoms persist for more than a few days, consult a doctro. If pregnant or breast-feeding, ask a doctor before use.

QUESTIONS

newtonlabs.net - Questions? 800 448-7256

Newton Laboratories, Inc. FDA Est # 1051203 - Conyers, GA 30013

INACTIVE INGREDIENT SECTION

Inactive Ingredients: USP Purified Water; USP Gluten-free, non-GMO, organic cane alcohol 20%.

OTC - PURPOSE SECTION

Formulated for symptoms associated with acne and other skin conditions such as boils, pimples, pustules and sebaceous cysts.

OTC - ACTIVE INGREDIENT SECTION

Equal parts of Echinacea 6x, Juglans regia 6x, Lappa 6x, Taraxacum 6x, Antimon. crud. 15x, Arsenicum alb. 15x, Aur. met. 15x, Berber. aqui. 15x, Bovista 15x, Carbo veg. 15x, Causticum 15x, Chelidonium maj. 15x, Dulcamara 15x, Graphites 15x, Hepar sulph. calc. 15x, Hydrocotyle 15x, Kali brom. 15x, Kali iod. 15x, Ledum 15x, Lycopodium 15x, Nux vom. 15x, Silicea 15x,Sulphur iod. 15x, Zinc. met. 15x.

DOSAGE & ADMINISTRATION SECTION

Directions: Ages 12 and up, take 6 drops by mouth (ages 0 to 11, give 3 drops) one to four times daily or as directed by a health professional. Sensitive persons begin with 1 drop and gradually increase to full dose.

INDICATIONS & USAGE SECTION

Formulated for symptoms associated with acne and other skin conditions such as boils, pimples, pustules and sebaceous cysts.